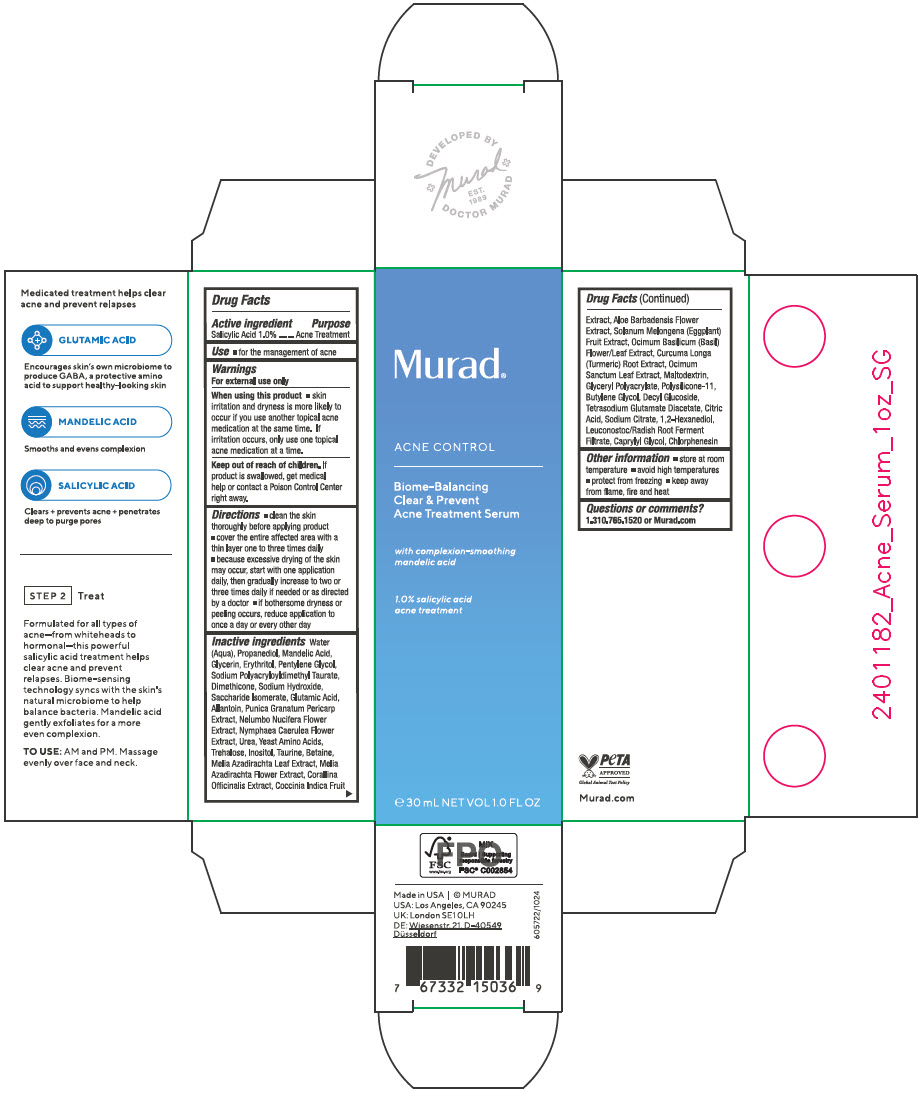 DRUG LABEL: Biome-Balancing Clear and Prevent Acne (Blemish) Treatment Serum
NDC: 70381-134 | Form: SOLUTION
Manufacturer: Murad, LLC
Category: otc | Type: HUMAN OTC DRUG LABEL
Date: 20250505

ACTIVE INGREDIENTS: SALICYLIC ACID 1 g/100 mL
INACTIVE INGREDIENTS: WATER; PROPANEDIOL; MANDELIC ACID; GLYCERIN; ERYTHRITOL; PENTYLENE GLYCOL; SODIUM POLYACRYLOYLDIMETHYL TAURATE; DIMETHICONE; SODIUM HYDROXIDE; SACCHARIDE ISOMERATE; GLUTAMIC ACID; ALLANTOIN; POMEGRANATE FRUIT RIND; NELUMBO NUCIFERA FLOWER; NYMPHAEA CAERULEA FLOWER; UREA; AMINO ACIDS, SOURCE UNSPECIFIED; TREHALOSE; INOSITOL; TAURINE; BETAINE; AZADIRACHTA INDICA LEAF; AZADIRACHTA INDICA FLOWER; CORALLINA OFFICINALIS; COCCINIA GRANDIS FRUIT; ALOE VERA FLOWER; EGGPLANT; OCIMUM BASILICUM FLOWERING TOP; TURMERIC; HOLY BASIL LEAF; MALTODEXTRIN; DIMETHICONE/VINYL DIMETHICONE CROSSPOLYMER (SOFT PARTICLE); BUTYLENE GLYCOL; DECYL GLUCOSIDE; TETRASODIUM GLUTAMATE DIACETATE; CITRIC ACID MONOHYDRATE; TRISODIUM CITRATE DIHYDRATE; 1,2-HEXANEDIOL; LEUCONOSTOC/RADISH ROOT FERMENT FILTRATE; CAPRYLYL GLYCOL; CHLORPHENESIN; POLYACRYLATE-13

Biome-Balancing Clear & Prevent Acne (Blemish) Treatment Serum

Drug Facts

Active ingredients

Salicylic Acid 1.0%

Purpose

Acne Treatment

Use

- for the management of acne

Warnings

For external use only

When using this product

- skin irritation and dryness is more likely to occur if you use another topical acne medication at the same time. If irritation occurs, only use one topical acne medication at a time.

Keep out of reach of children. If product is swallowed, get medical help or contact a Poison Control Center right away.

Directions

- clean the skin thoroughly before applying product
- cover the entire affected area with a thin layer one to three times daily
- because excessive drying of the skin may occur, start with one application daily, then gradually increase to two or three times daily if needed or as directed by a doctor
- if bothersome dryness or peeling occurs, reduce application to once a day or every other day

Inactive ingredients

Water (Aqua), Propanediol, Mandelic Acid, Glycerin, Erythritol, Pentylene Glycol, Sodium Polyacryloyldimethyl Taurate, Dimethicone, Sodium Hydroxide, Saccharide Isomerate, Glutamic Acid, Allantoin, Punica Granatum Pericarp Extract, Nelumbo Nucifera Flower Extract, Nymphaea Caerulea Flower Extract, Urea, Yeast Amino Acids, Trehalose, Inositol, Taurine, Betaine, Melia Azadirachta Leaf Extract, Melia Azadirachta Flower Extract, Corallina Officinalis Extract, Coccinia Indica Fruit Extract, Aloe Barbadensis Flower Extract, Solanum Melongena (Eggplant) Fruit Extract, Ocimum Basilicum (Basil) Flower/Leaf Extract, Curcuma Longa (Turmeric) Root Extract, Ocimum Sanctum Leaf Extract, Maltodextrin, Glyceryl Polyacrylate, Polysilicone-11, Butylene Glycol, Decyl Glucoside, Tetrasodium Glutamate Diacetate, Citric Acid, Sodium Citrate, 1,2-Hexanediol, Leuconostoc/Radish Root Ferment Filtrate, Caprylyl Glycol, Chlorphenesin

Other information

- store at room temperature
- avoid high temperatures
- protect from freezing
- keep away from flame, fire and heat

Questions or comments?

1.310.765.1520 or Murad.com

PRINCIPAL DISPLAY PANEL - 30 mL Bottle Carton

Murad®

ACNE CONTROL

Biome-Balancing
Clear & Prevent
Acne Treatment Serum

with complexion-smoothing
mandelic acid

1.0% salicylic acid
acne treatment

℮ 30 mL NET VOL 1.0 FL OZ